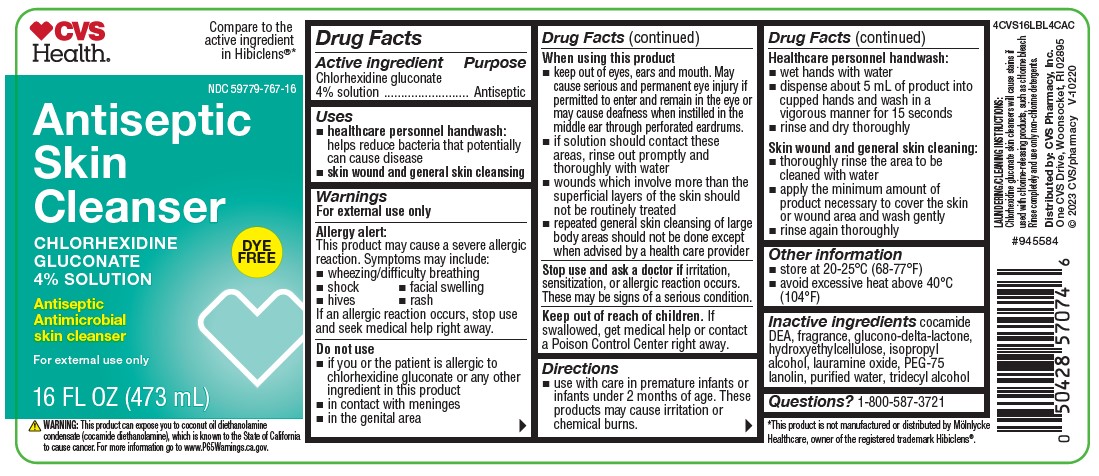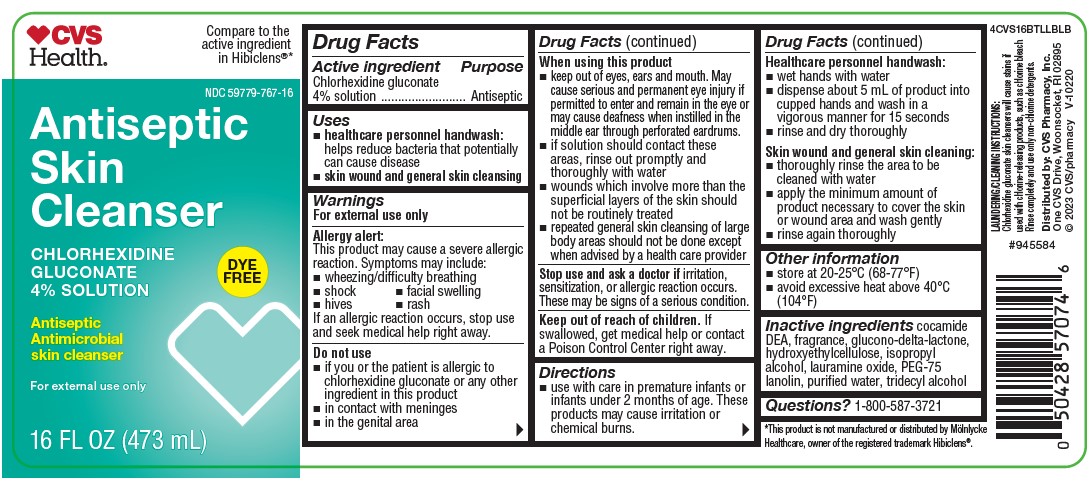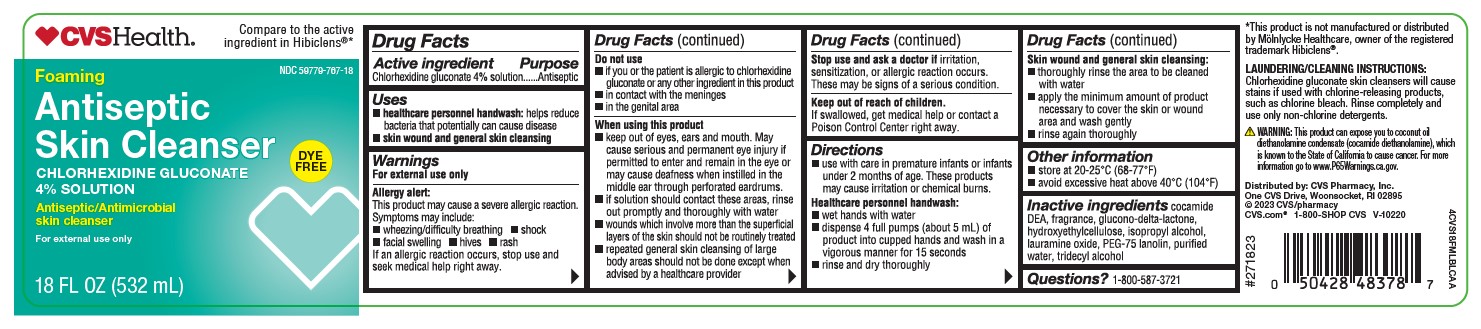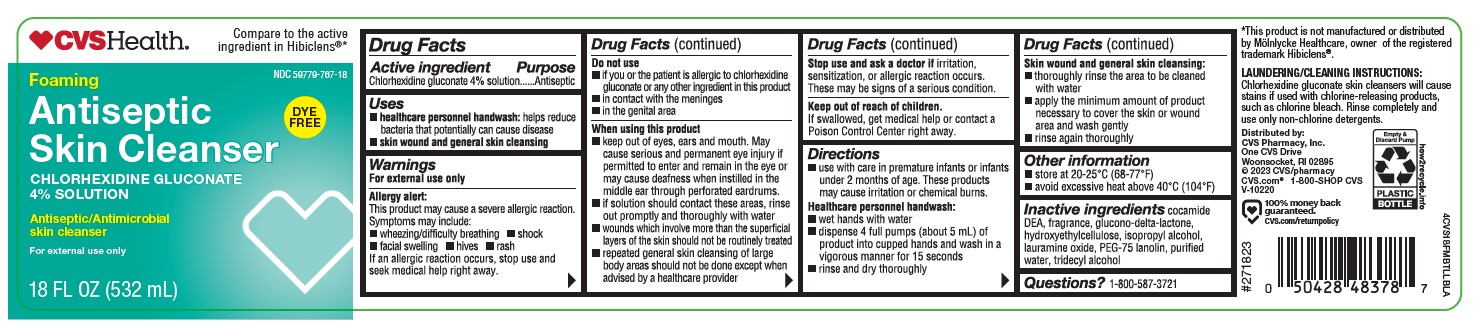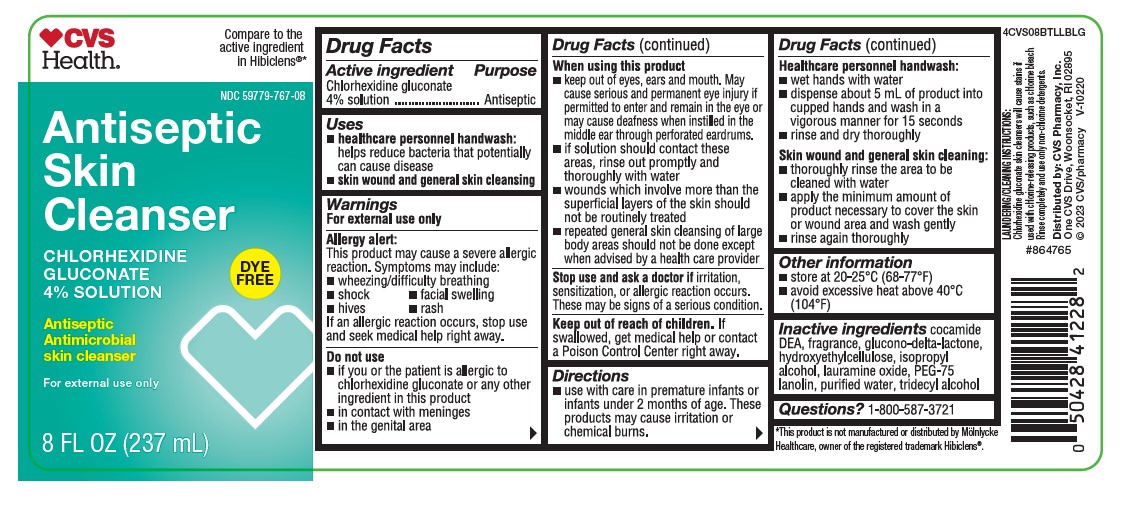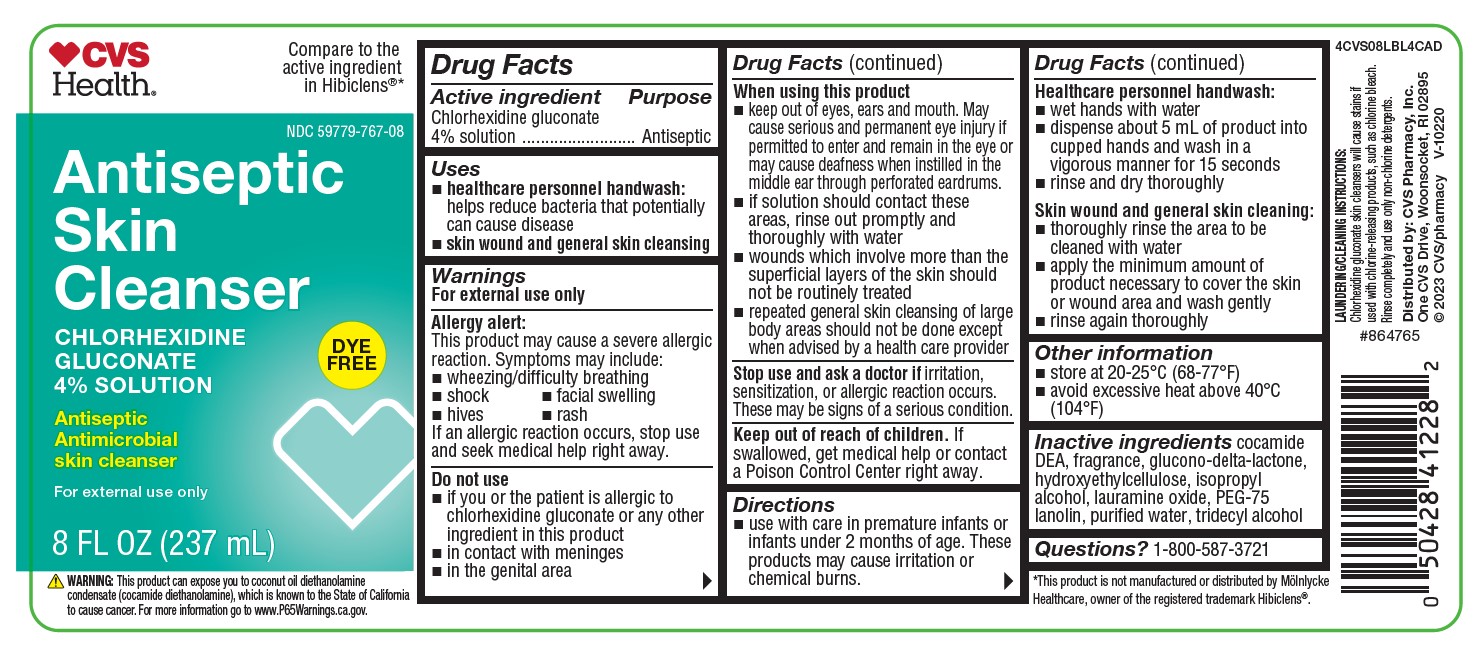 DRUG LABEL: Antiseptic Skin Cleanser
NDC: 59779-767 | Form: LIQUID
Manufacturer: CVS Pharmacy, Inc.
Category: otc | Type: HUMAN OTC DRUG LABEL
Date: 20251212

ACTIVE INGREDIENTS: CHLORHEXIDINE GLUCONATE 4 g/100 mL
INACTIVE INGREDIENTS: GLUCONOLACTONE; PEG-75 LANOLIN; TRIDECYL ALCOHOL; COCO DIETHANOLAMIDE; HYDROXYETHYL CELLULOSE (2000 CPS AT 1%); ISOPROPYL ALCOHOL; LAURAMINE OXIDE; WATER

CVS 4% 8oz, 8oz CA, 16oz, 16oz CA, 18oz, 18oz CA
COMP 18oz, 18oz CA

ACTIVE INGREDIENT

Chlorhexidine gluconate 4% Solution

Purpose

Antiseptic

Uses

- healthcare personnel handwash: helps reduce bacteria that potentially can cause disease
- skin wound and general cleansing

Warnings

For external use only

Allergy alert:

This product may cause a severe allergic reaction. Symptoms may include:

- wheezing
- shock
- facial swelling
- hives
- rash

If an allergic reaction occurs, stop use and seek medical help right away.

Do not use

- if you or the patient is allergic to chlorhexidine gluconate or any other ingredient in this product
- in contact with meninges
- in the genital area

When using this product

- keep out of eyes, ears, and mouth. May cause serious and permanent eye injury if permitted to enter and remain in the eye or may cause deafness when instilled in the middle ear through perforated eardrums
- if solution should contact these areas, rinse out promptly and thoroughly with water
- wound which involve more than the superficial layers of the skin should not be routinely treated
- repeated general skin cleansing of large body areas should not be done except when the advised by a health care provider

Stop use and ask a doctor

if irritation, sensitization, or allergic reaction occurs. These may be signs of a serious condition.

Keep out of reach of children

If swallowed, get medical help or contact a Poison Control Center right away.

Directions

- use with care in premature infants or infants under 2 months of age. These products may cause irritation or chemical burns.

Healthcare personnel handwash:

- wet hands with water
- dispense about 5 ml of product into cupped hands and wash in a vigorous manner for 15 seconds
- rinse and dry thoroughly

Skin wound and general skin cleansing:

- thoroughly rinse the area to be cleaned with water
- apply the minimum amount of product necessary to cover the skin or wound area and wash gently
- rinse again thoroughly

other information

- store at 20-25 C (68-77 F)
- avoid excessive heat above 40 C (104 F)

Inactive ingredients

cocamide DEA, fragrance, glucono-delta-lactone, hydroxyethylcellulose, isopropyl alcohol, lauramine oxide, PEG-75 lanolin, purified water, tridecyl alcohol

OTHER SAFETY INFORMATION

*This product is not manufactured or distributed by Mölnlycke Healthcare, owner of the registered trademark Hibiclens®.

Warning: This product can expose you to coconut oil diethanolamine condensate (cocamide diethanolamine), which is known to the State of California to cause cancer. For more information go to www.P65Warnings.gov

Laundering/Cleaning Instructions: Chlorhexidine gluconate skin cleansers will cause stains if used with chlorine releasing products. Rinse completely and use only non-chlorine detergents.

RECENT MAJOR CHANGES

Uses: removal of surgical handscub indication (11/23)

Directions : removal of surgical handscrub indication (11/23)

Questions?

1-800-587-3721

Packaging

CVS Health Compare to the active ingredient in Hibiclens®*

NDC 59779-767-08

Chlorhexidine Gluconate 4% Solution

Antiseptic Skin Cleanser

Antiseptic Antimicrobial skin cleanser

For external use only

Dye Free

Distributed by:

CVS Pharmacy, Inc.

Woonsocket, RI 02985

©2023 CVS/pharmacy V-10220

4CVS08BTLLBLG

8FL OZ (237mL)

This product is not manufactured or distributed
by Mölnlycke Healthcare, owner of the registered
trademark Hibiclens®.

4CVS08LBL4CAD

WARNING: This product can expose you to coconut oil diethanolamine condensate (cocamide diethanolamine), which is known to the State of California to cause cancer. For more information go to www.P65Warnings.ca.gov.

CVS Health Compare to the active ingredient in Hibiclens®*

NDC 59779-767-16

Chlorhexidine Gluconate 4% Solution

Antiseptic Skin Cleanser

Antiseptic Antimicrobial skin cleanser

For external use only

Dye Free

Distributed by:

CVS Pharmacy, Inc.

Woonsocket, RI 02985

© 2023 CVS/pharmacy V-10220

4CVS16BTLLBLA

16FL OZ (473mL)

This product is not manufactured or distributed
by Mölnlycke Healthcare, owner of the registered
trademark Hibiclens®.

4CVS16LBL4CAC

WARNING: This product can expose you to coconut oil diethanolamine condensate (cocamide diethanolamine), which is known to the State of California to cause cancer. For more information go to www.P65Warnings.ca.gov.

CVS Health Compare to the active ingredient in Hibiclens®*

NDC 59779-767-18

Chlorhexidine Gluconate 4% Solution

Antiseptic Skin Cleanser

Antiseptic Antimicrobial skin cleanser

For external use only

Dye Free

Distributed by:

CVS Pharmacy, Inc.

Woonsocket, RI 02985

4CVS18FMBTLLBLA

18FL OZ (532mL)

© 2023 CVS/pharmacy
CVS.com® 1-800-SHOP CVS

This product is not manufactured or distributed
by Mölnlycke Healthcare, owner of the registered
trademark Hibiclens®.

how2recycle.info

100% money back gurantee. CVS.com/returnpolicy

4CVS18FMLBLCAA

WARNING: This product can expose you to coconut oil diethanolamine condensate (cocamide diethanolamine), which is known to the State of California to cause cancer. For more information go to www.P65Warnings.ca.gov.